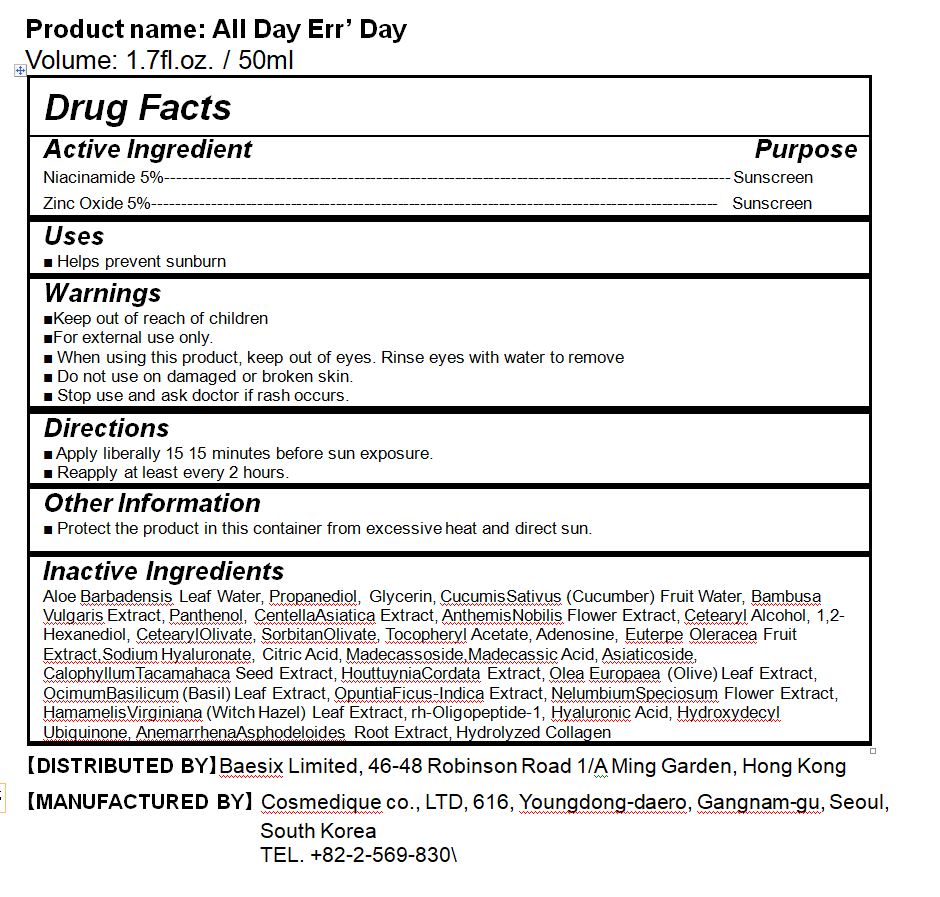 DRUG LABEL: All Day Err Day
NDC: 74921-0002 | Form: LIQUID
Manufacturer: COSMEDIQUE CO.,LTD.
Category: otc | Type: HUMAN OTC DRUG LABEL
Date: 20211023

ACTIVE INGREDIENTS: ZINC OXIDE 5 g/100 mL; NIACINAMIDE 5 g/100 mL
INACTIVE INGREDIENTS: PANTHENOL; GLYCERIN

Drug Facts

ACTIVE INGREDIENT

niacinamide, zinc oxide

INACTIVE INGREDIENT

Aloe Barbadensis Leaf Water
Propanediol
Niacinamide
Glycerin
Zinc Oxide
Cucumis Sativus (Cucumber) Fruit Water
Bambusa Vulgaris Extract
Panthenol
Centella Asiatica Extract
Anthemis Nobilis Flower Extract
Cetearyl Alcohol
1,2-Hexanediol
Cetearyl Olivate
Sorbitan Olivate
Tocopheryl Acetate
Adenosine
Euterpe Oleracea Fruit Extract
Sodium Hyaluronate
Citric Acid
Madecassoside
Madecassic Acid
Asiaticoside
Calophyllum Tacamahaca Seed Extract
Houttuynia Cordata Extract
Olea Europaea (Olive) Leaf Extract
Ocimum Basilicum (Basil) Leaf Extract
Opuntia Ficus-Indica Extract
Nelumbium Speciosum Flower Extract
Hamamelis Virginiana (Witch Hazel) Leaf Extract

Hyaluronic Acid
Hydroxydecyl Ubiquinone
Anemarrhena Asphodeloides Root Extract
Collagen Extract

rh-Oligopeptide-1

PURPOSE

Helps prevent sunburn

KEEP OUT OF REACH OF THE CHILDREN

INDICATIONS AND USAGE

■ Apply liberally 15 15 minutes before sun exposure.

■ Reapply at least every 2 hours.

WARNINGS

For external use only.

Flammable, keep away from fire or flame.

When using this product keep out of eyes. If contact with eyes occurs, rinse promptly and thoroughly with water.

Stop use and ask a doctor if significant irritation or sensitization develops.

Keep out of reach of children. If swallowed, get medical help or contact a Poison Control Center right away.

DOSAGE AND ADMINISTRATION

external use only